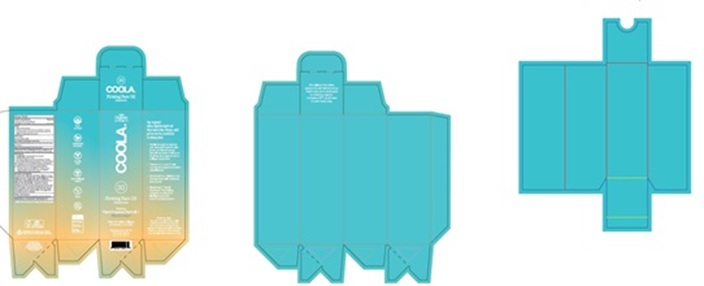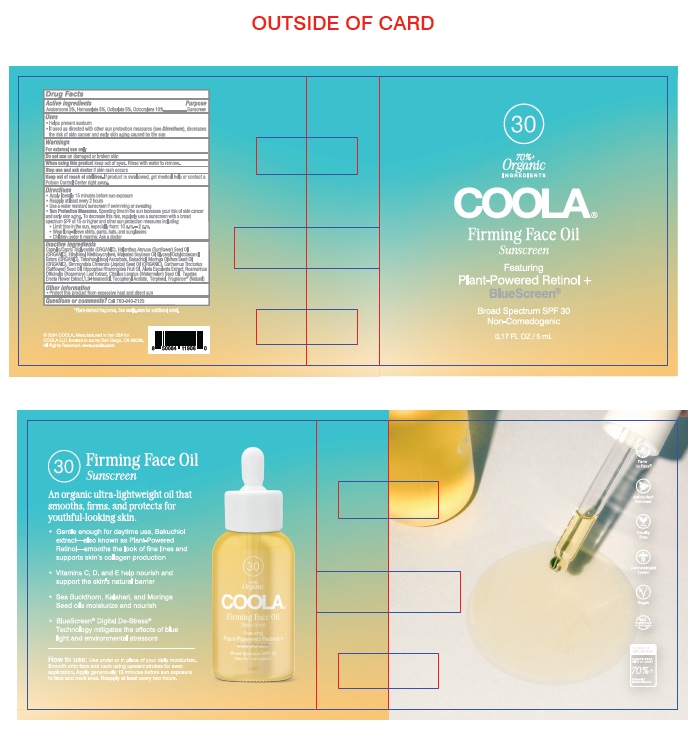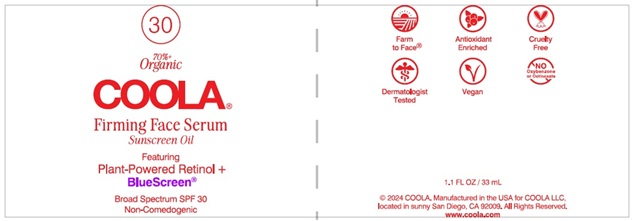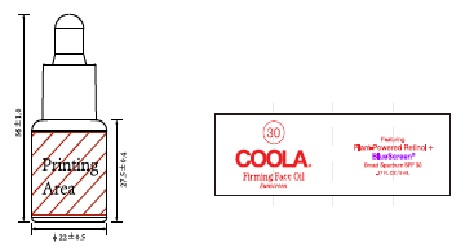 DRUG LABEL: COOLA Firming Face Serum Sunscreen
NDC: 79753-083 | Form: OIL
Manufacturer: COOLA LLC
Category: otc | Type: HUMAN OTC DRUG LABEL
Date: 20250306

ACTIVE INGREDIENTS: AVOBENZONE 3.0 g/100 mL; HOMOSALATE 5.0 g/100 mL; OCTISALATE 5.0 g/100 mL; OCTOCRYLENE 10.0 g/100 mL
INACTIVE INGREDIENTS: CAPRYLIC/CAPRIC TRIGLYCERIDE; HELIANTHUS ANNUUS (SUNFLOWER) SEED OIL; ETHYLHEXYL METHOXYCRYLENE; SOYBEAN OIL; TETRAHEXYLDECYL ASCORBATE; BAKUCHIOL; MORINGA OLEIFERA SEED OIL; SIMMONDSIA CHINENSIS (JOJOBA) SEED OIL; CARTHAMUS TINCTORIUS (SAFFLOWER) SEED OIL; HIPPOPHAE RHAMNOIDES FRUIT OIL; ALARIA ESCULENTA; ROSEMARY; Citrullus Lanatus (Watermelon) Seed Oil; TAGETES ERECTA FLOWER; 1,2-HEXANEDIOL; .ALPHA.-TOCOPHEROL ACETATE; TERPINEOL

COOLA Firming Face Serum Sunscreen Oil SPF 30

Active Ingredients

AVOBENZONE 3%, HOMOSALATE 5%, OCTISALATE 5%, OCTOCRYLENE 10%

Purpose

Sunscreen

Uses
• helps prevent sunburn
• if used as directed with other sun protection measures
(see Directions) decreases the risk of skin cancer and
early aging caused by the sun

Warnings

For external use only

Do not use on damaged or broken skin

When using this product keep out of eyes. Rinse with water to remove

Stop use and ask doctor if skin rash occurs

Keep out of reach of children. If product is swallowed, get medical help or contact a Poison Control Center right away.

Directions

● Apply liberally 15 minutes before sun exposure

● Reapply at least every 2 hours

● Use a water resistant sunscreen especially if swimming or sweating

● Sun Protection Measures. Spending time in the sun increases

your risk of skin cancer and early aging. To decrease this

risk, regularly use a sunscreen with a broad spectrum SPF of 15

or higher and other sun protection measures including:
● Limit time in the sun, especially from: 10 a.m. – 2 p.m.
● Wear long-sleve shirts, pants, hats, and sunglasses

● Children under 6 months: Ask a doctor

Inactive Ingredients
Caprylic/Capric Triglyceride(ORGANIC), Helianthus Annuus
(Sunflower) Seed Oil (ORGANIC), Ethylhexyl Methoxycrylene,
Maleated Soybean Oil Glyceryl/Octyldodecanol Esters
(ORGANIC), Tetrahexyldecyl Ascorbate, Bakuchiol, Moringa
Oleifera Seed Oil (ORGANIC), Simmondsia Chinensis
(Jojoba) Seed Oil (ORGANIC), Carthamus Tinctorius
(Safflower) Seed Oil, Hippophae Rhamnoides Fruit Oil, Alaria
Esculenta Extract, Rosmarinus Officinalis (Rosemary) Leaf
Extract, Citrullus Lanatus (Watermelon) Seed Oil, Tagetes
Erecta Flower Extract, 1,2-Hexanediol, Tocopheryl Acetate,
Terpineol, Fragrance* (Natural)

Other Information

● Protect this product from excessive heat and direct sun

Questions or comments? Call 760-940-2125

-------------------

Product Labeling - COOLA Firming Face Oil Sunscreen SPF 30

COOLA Firming Face Oil

Sunscreen

Broad Spectrum SPF 30

1.1 FL OZ / 33 mL

2024 COOLA.

Manufactured in the USA for

COOLA LLC, located in Sunny

San Diego, CA 92009.

All Rights Reserved.

www.coola.com

33 mL Carton

33 mLBottle

5 mL Sample Card

5 mL Sample Bottle

res